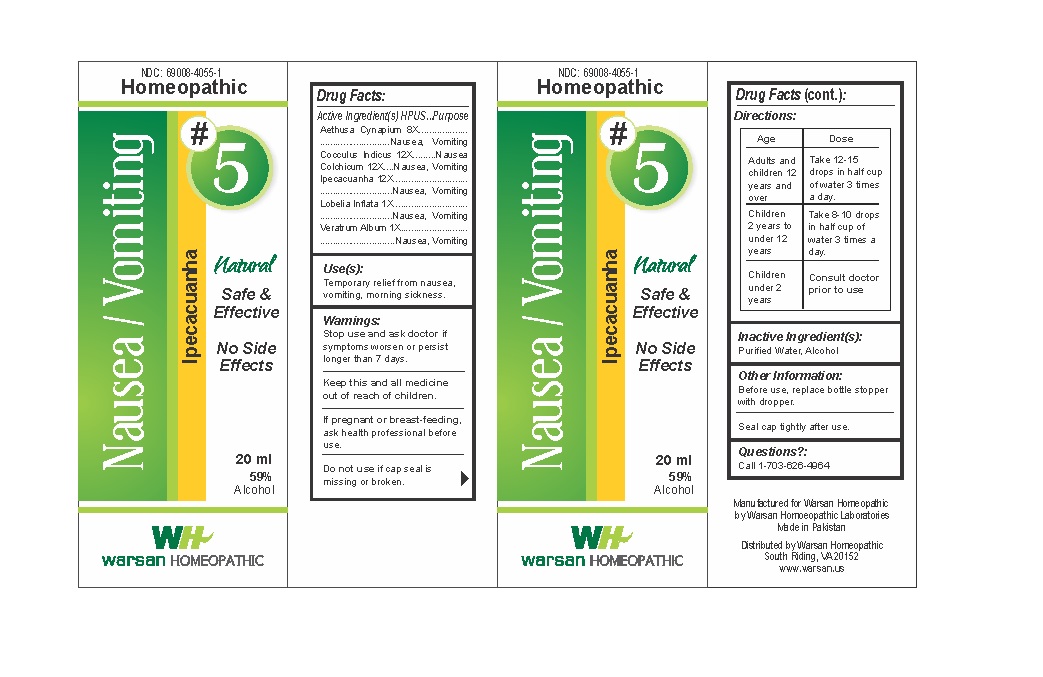 DRUG LABEL: Combo Remedy 5 - Nausea Vomiting
NDC: 69008-4055 | Form: SOLUTION/ DROPS
Manufacturer: Warsan Homoeopathic
Category: homeopathic | Type: HUMAN OTC DRUG LABEL
Date: 20171225

ACTIVE INGREDIENTS: VERATRUM ALBUM ROOT 1 [hp_X]/1 mL; COLCHICUM AUTUMNALE BULB 12 [hp_X]/1 mL; IPECAC 12 [hp_X]/1 mL; LOBELIA INFLATA 1 [hp_X]/1 mL; AETHUSA CYNAPIUM 8 [hp_X]/1 mL; ANAMIRTA COCCULUS SEED 12 [hp_X]/1 mL
INACTIVE INGREDIENTS: WATER; ALCOHOL

Keep out of reach of children.

Stop use and ask doctor if symptoms worsen or persist longer than 7 days.

If pregnant or breast-feeding, ask health professional before use.

Do not use if tamper evident seal is missing or broken.

ACTIVE INGREDIENT

Aethusa Cynapium 8X

Cocculus Indicus 12X

Colchicum 12X

Ipecacuanha 12X

Lobelia Inflata 1X

Veratrum Album 1X

PURPOSE

Temporary relief from nausea, vomiting, morning sickness.

INACTIVE INGREDIENT

Purified Water

Alcohol

DOSAGE AND ADMINISTRATION

Adults and children 12 years and older: Take 10-15 drops in half cup of water 3 times a day.

Children 2 years to under 12 years: Take 8-10 drops in half cup of water of 3 times a day.

Children under 2 years: Consult doctor prior to use.

INDICATIONS AND USAGE

Temporary relief from nausea, vomiting, morning sickness.